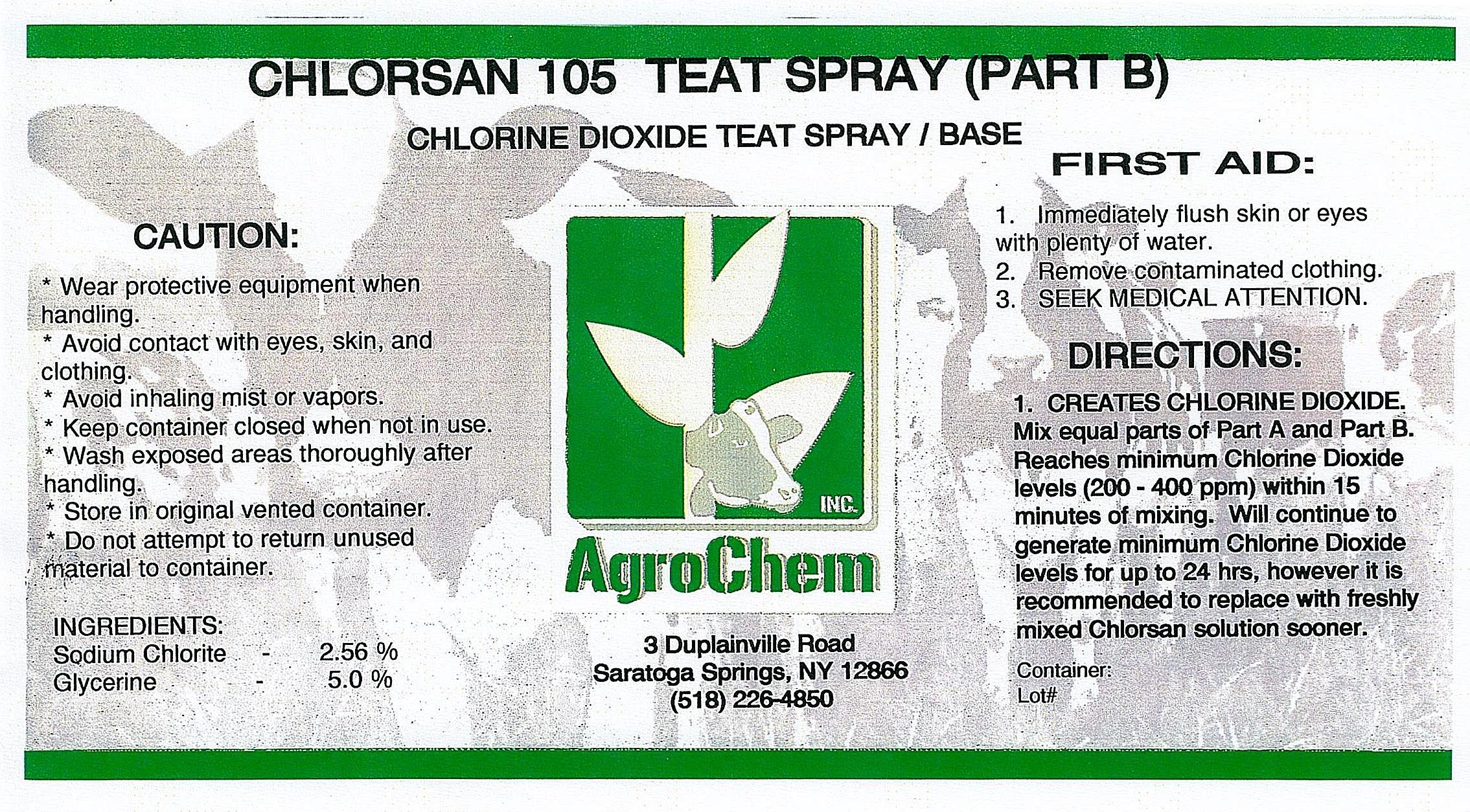 DRUG LABEL: Chlorsan 105 Part B
NDC: 17307-3653 | Form: SPRAY
Manufacturer: AgroChem Inc
Category: animal | Type: OTC ANIMAL DRUG LABEL
Date: 20130927

ACTIVE INGREDIENTS: SODIUM CHLORITE 0.0256 kg/1 kg
INACTIVE INGREDIENTS: WATER 0.0924 kg/1 kg; GLYCERIN 0.05 kg/1 kg

Chlorsan 105 Part B

DESCRIPTION

CHLORINE DIOXIDE TEAT SPRAY/BASE

WARNINGS AND PRECAUTIONS

CAUTION:

* Wear protective equipment when

handling.

* Avoid contact with eyes, skin, and

clothing.

* Avoid inhaling mist or vapors.

* Keep container closed when not in use.

* Wash exposed areas thoroughly after

handling.

* Store in original vented container.

* Do not attempt to return unused

material to container.

ACTIVE INGREDIENT

INGREDIENTS:

Sodium Chlortie - 2.56%

Glycerine - 5.0%

USER SAFETY WARNINGS

FIRST AID:

1. Immediately flush skin or eyes

with plenty of water.

2. Remove contaminated clothing.

3. SEEK MEDICAL ATTENTION.

DIRECTIONS:

1. CREATES CHLORINE DIOXIDE.

Mix equal parts of Part A and Part B.

Reaches minimum Chlorine Dioxide

levels (200 - 400 ppm) within 15

minutes of mixing. Will continue to

generate minimum Chorine Dioxide

levels for up to 24 hrs, however it is

recommended to replace with freshly

mixed Chlorsan solution sooner.